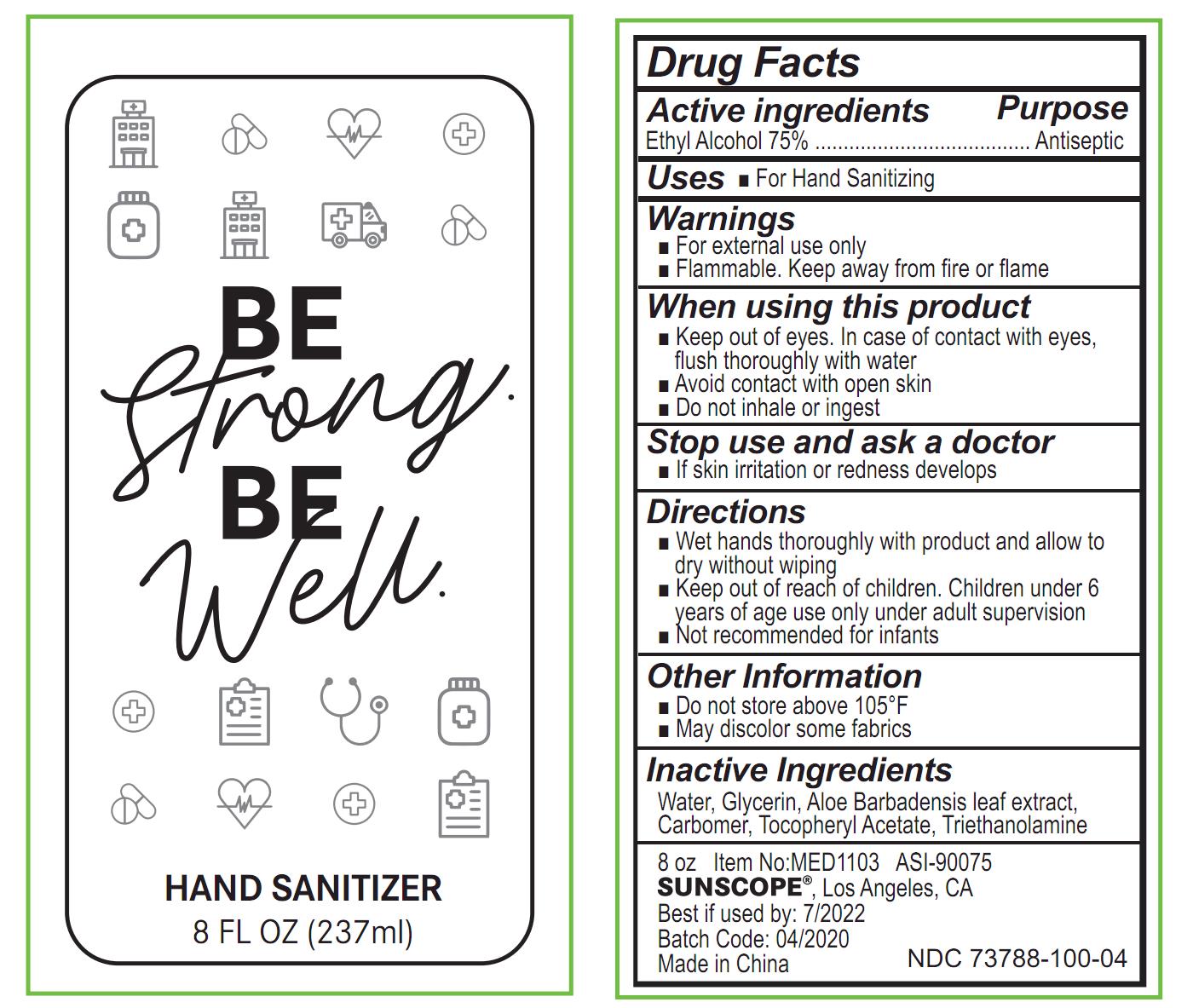 DRUG LABEL: hand sanitizer
NDC: 73788-100 | Form: GEL
Manufacturer: Hangzhou Huiji Biotechnology Co., Ltd.
Category: otc | Type: HUMAN OTC DRUG LABEL
Date: 20220224

ACTIVE INGREDIENTS: ALCOHOL 75 mL/100 mL
INACTIVE INGREDIENTS: WATER; GLYCERIN; ALOE VERA LEAF; TROLAMINE; CARBOMER 934; .ALPHA.-TOCOPHEROL ACETATE

73788-100 hand sanitizer

Active Ingredient

Ethyl Alcohol 70%

Purpose

Antiseptic

Use

For Hand Sanitizing

WARNINGS

Keep out of eyes. In case of contact with eyes,
flush thoroughly with water
Avoid contact with open skin
Do not inhale or ingest
Stop use and ask a doctor
If skin iritation or redness develops

■Keep out of reach of children. Children under 6
years of age use only under adult supervision
■Not recommended for infants

Directions

Wet hands thoroughly with product and allow to dry without wiping

Other Information

1 Do not store above 105°F
1 May discolor some fabrics

Inactive ingredients

Alcohol, Water (Aqua), Glycerin, Butylene Glycol, Carbomer,
Aminomethyl Propanol, Aloe Barbadensis Leaf Extract